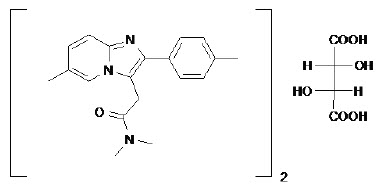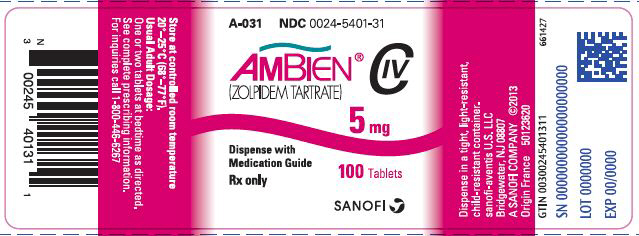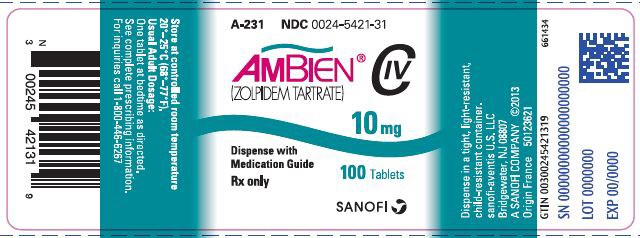 DRUG LABEL: Ambien
NDC: 0024-5401 | Form: TABLET, FILM COATED
Manufacturer: Sanofi-Aventis U.S. LLC
Category: prescription | Type: HUMAN PRESCRIPTION DRUG LABEL
Date: 20250415
DEA Schedule: CIV

ACTIVE INGREDIENTS: ZOLPIDEM TARTRATE 5 mg/1 1
INACTIVE INGREDIENTS: HYPROMELLOSE, UNSPECIFIED; LACTOSE, UNSPECIFIED FORM; MAGNESIUM STEARATE; MICROCRYSTALLINE CELLULOSE; POLYETHYLENE GLYCOL, UNSPECIFIED; TITANIUM DIOXIDE; SODIUM STARCH GLYCOLATE TYPE A CORN; FD&C RED NO. 40; FERRIC OXIDE RED; POLYSORBATE 80

HIGHLIGHTS OF PRESCRIBING INFORMATION

These highlights do not include all the information needed to use AMBIEN safely and effectively. See full prescribing information for AMBIEN.
AMBIEN® (zolpidem tartrate) tablets, for oral use, C-IV
Initial U.S. Approval: 1992

WARNING: COMPLEX SLEEP BEHAVIORS

See full prescribing information for complete boxed warning.

Complex sleep behaviors including sleep-walking, sleep-driving, and engaging in other activities while not fully awake may occur following use of AMBIEN. Some of these events may result in serious injuries, including death. Discontinue AMBIEN immediately if a patient experiences a complex sleep behavior. (4, 5.1)

RECENT MAJOR CHANGES

Dosage and Administration (2.1) | 2/2022
Warnings and Precautions (5.5) | 2/2022
Warnings and Precautions (5.7) | 2/2022

1 INDICATIONS AND USAGE

AMBIEN, a gamma-aminobutyric acid (GABA) A receptor positive modulator, is indicated for the short-term treatment of insomnia characterized by difficulties with sleep initiation. (1)

2 DOSAGE AND ADMINISTRATION

- Use the lowest dose effective for the patient and must not exceed a total of 10 mg daily (2.1)
- Treatment should be as short as possible (2.1)
- Recommended initial dose is a single dose of 5 mg for women and a single dose of 5 or 10 mg for men, immediately before bedtime with at least 7–8 hours remaining before the planned time of awakening (2.1)
- Geriatric patients and patients with mild to moderate hepatic impairment: Recommended dose is 5 mg for men and women (2.2)
- Lower doses of CNS depressants may be necessary when taken concomitantly with AMBIEN (2.3)
- The effect of AMBIEN may be slowed if taken with or immediately after a meal (2.4)

3 DOSAGE FORMS AND STRENGTHS

5 mg and 10 mg tablets. Tablets not scored. (3)

4 CONTRAINDICATIONS

- Patients who have experienced complex sleep behaviors after taking AMBIEN (4)
- Known hypersensitivity to zolpidem (4)

5 WARNINGS AND PRECAUTIONS

- CNS-Depressant Effects: Impaired alertness and motor coordination including risk of morning impairment. Risk increases with dose and use with other CNS depressants and alcohol. Caution patients against driving and other activities requiring mental alertness the morning after use. Instruct patients on correct use. (5.2)
- Need to Evaluate for Comorbid Diagnoses: Reevaluate if insomnia persists after 7 to 10 days of use. (5.3)
- Severe Anaphylactic/Anaphylactoid Reactions: Angioedema and anaphylaxis have been reported. Do not rechallenge if such reactions occur. (5.4)
- Abnormal Thinking and Behavioral Changes: Changes including decreased inhibition, bizarre behavior, agitation, and depersonalization have been reported. Immediately evaluate any new onset behavioral changes. (5.5)
- Depression: Worsening of depression or suicidal thinking may occur. Prescribe the least amount of tablets feasible to avoid intentional overdose. (5.6)
- Respiratory Depression: Consider this risk before prescribing in patients with compromised respiratory function. (5.7)
- Hepatic Impairment: Avoid AMBIEN use in patients with severe hepatic impairment. (5.8)
- Withdrawal Effects: Symptoms may occur with rapid dose reduction or discontinuation. (5.9, 9.3)

6 ADVERSE REACTIONS

Most commonly observed adverse reactions were:

Short-term (<10 nights): Drowsiness, dizziness, and diarrhea

Long-term (28–35 nights): Dizziness and drugged feelings (6.1)

To report SUSPECTED ADVERSE REACTIONS, contact sanofi-aventis U.S. LLC at 1-800-633-1610 or FDA at 1-800-FDA-1088 or www.fda.gov/medwatch.

7 DRUG INTERACTIONS

- CNS depressants, including alcohol: Possible adverse additive CNS-depressant effects (5.2, 7.1)
- Opioids: Concomitant use may increase risk of respiratory depression (5.7, 7.1)
- Imipramine: Decreased alertness observed (7.1)
- Chlorpromazine: Impaired alertness and psychomotor performance observed (7.1)
- CYP3A4 inducers (rifampin or St. John's wort): Combination use may decrease effect (7.2)
- Ketoconazole: Combination use may increase effect (7.2)

8 USE IN SPECIFIC POPULATIONS

- Pregnancy: May cause respiratory depression and sedation in neonates with exposure late in the third trimester. (8.1)
- Lactation: A lactating woman may pump and discard breast milk during treatment and for 23 hours after AMBIEN administration. (8.2)
- Pediatric use: Safety and effectiveness not established. Hallucinations (incidence rate 7%) and other psychiatric and/or nervous system adverse reactions were observed frequently in a study of pediatric patients with Attention-Deficit/Hyperactivity Disorder. (5.5, 8.4)

FULL PRESCRIBING INFORMATION

WARNING: COMPLEX SLEEP BEHAVIORS

Complex sleep behaviors including sleep-walking, sleep-driving, and engaging in other activities while not fully awake may occur following use of AMBIEN. Some of these events may result in serious injuries, including death. Discontinue AMBIEN immediately if a patient experiences a complex sleep behavior [see Contraindications (4) and Warnings and Precautions (5.1)].

1 INDICATIONS AND USAGE

AMBIEN (zolpidem tartrate) is indicated for the short-term treatment of insomnia characterized by difficulties with sleep initiation. AMBIEN has been shown to decrease sleep latency for up to 35 days in controlled clinical studies [see Clinical Studies (14)].

The clinical trials performed in support of efficacy were 4–5 weeks in duration with the final formal assessments of sleep latency performed at the end of treatment.

2 DOSAGE AND ADMINISTRATION

2.1 Dosage in Adults

Use the lowest effective dose for the patient. The recommended initial dose is 5 mg for women and either 5 or 10 mg for men, taken only once per night immediately before bedtime with at least 7–8 hours remaining before the planned time of awakening. If the 5 mg dose is not effective, the dose can be increased to 10 mg. In some patients, the higher morning blood levels following use of the 10 mg dose increase the risk of next-day impairment of driving and other activities that require full alertness [see Warnings and Precautions (5.2)]. The total dose of AMBIEN should not exceed 10 mg once daily immediately before bedtime. AMBIEN should be taken as a single dose and should not be readministered during the same night.

The recommended initial doses for women and men are different because zolpidem clearance is lower in women.

Long-term use of AMBIEN is not recommended. Treatment should be as short as possible. Extended treatment should not take place without re-evaluation of the patient's status because the risk of abuse and dependence increases with the duration of treatment [see Drug Abuse and Dependence (9.3)].

2.2 Special Populations

Elderly or debilitated patients may be especially sensitive to the effects of zolpidem tartrate. The recommended dose of AMBIEN in these patients is 5 mg once daily immediately before bedtime [see Warnings and Precautions (5.2), Use in Specific Populations (8.5)].

Patients with mild to moderate hepatic impairment do not clear the drug as rapidly as normal subjects. The recommended dose of AMBIEN in these patients is 5 mg once daily immediately before bedtime. Avoid AMBIEN use in patients with severe hepatic impairment as it may contribute to encephalopathy [see Warnings and Precautions (5.8), Use in Specific Populations (8.7), Clinical Pharmacology (12.3)].

2.3 Use with CNS Depressants

Dosage adjustment may be necessary when AMBIEN is combined with other CNS-depressant drugs because of the potentially additive effects [see Warnings and Precautions (5.2, 5.7)].

2.4 Administration

The effect of AMBIEN may be slowed by ingestion with or immediately after a meal.

3 DOSAGE FORMS AND STRENGTHS

AMBIEN is available in 5 mg and 10 mg strength tablets for oral administration. Tablets are not scored.

AMBIEN 5 mg tablets are capsule-shaped, pink, film coated, with AMB 5 debossed on one side and 5401 on the other.

AMBIEN 10 mg tablets are capsule-shaped, white, film coated, with AMB 10 debossed on one side and 5421 on the other.

4 CONTRAINDICATIONS

AMBIEN is contraindicated in patients

- who have experienced complex sleep behaviors after taking AMBIEN [see Warnings and Precautions (5.1)].
- with known hypersensitivity to zolpidem. Observed reactions include anaphylaxis and angioedema [see Warnings and Precautions (5.4)].

5 WARNINGS AND PRECAUTIONS

5.1 Complex Sleep Behaviors

Complex sleep behaviors, including sleep-walking, sleep-driving, and engaging in other activities while not fully awake, may occur following the first or any subsequent use of AMBIEN. Patients can be seriously injured or injure others during complex sleep behaviors. Such injuries may result in a fatal outcome. Other complex sleep behaviors (e.g., preparing and eating food, making phone calls, or having sex) have also been reported. Patients usually do not remember these events. Postmarketing reports have shown that complex sleep behaviors may occur with AMBIEN alone at recommended doses, with or without the concomitant use of alcohol or other central nervous system (CNS) depressants [see Drug Interactions (7.1)]. Discontinue AMBIEN immediately if a patient experiences a complex sleep behavior [see Contraindications (4)].

5.2 CNS-Depressant Effects and Next-Day Impairment

AMBIEN, like other sedative-hypnotic drugs, has CNS-depressant effects. Coadministration with other CNS depressants (e.g., benzodiazepines, opioids, tricyclic antidepressants, alcohol) increases the risk of CNS depression [see Drug Interactions (7.1)]. Dosage adjustments of AMBIEN and of other concomitant CNS depressants may be necessary when AMBIEN is administered with such agents because of the potentially additive effects. The use of AMBIEN with other sedative-hypnotics (including other zolpidem products) at bedtime or the middle of the night is not recommended [see Dosage and Administration (2.3)].

The risk of next-day psychomotor impairment, including impaired driving, is increased if AMBIEN is taken with less than a full night of sleep remaining (7 to 8 hours); if a higher than the recommended dose is taken; if coadministered with other CNS depressants or alcohol; or if coadministered with other drugs that increase the blood levels of zolpidem. Patients should be warned against driving and other activities requiring complete mental alertness if AMBIEN is taken in these circumstances [see Dosage and Administration (2), Clinical Studies (14.3)].

Vehicle drivers and machine operators should be warned that, as with other hypnotics, there may be a possible risk of adverse reactions including drowsiness, prolonged reaction time, dizziness, sleepiness, blurred/double vision, reduced alertness, and impaired driving the morning after therapy. In order to minimize this risk a full night of sleep (7–8 hours) is recommended.

Because AMBIEN can cause drowsiness and a decreased level of consciousness, patients, particularly the elderly, are at higher risk of falls.

5.3 Need to Evaluate for Comorbid Diagnoses

Because sleep disturbances may be the presenting manifestation of a physical and/or psychiatric disorder, symptomatic treatment of insomnia should be initiated only after a careful evaluation of the patient. The failure of insomnia to remit after 7 to 10 days of treatment may indicate the presence of a primary psychiatric and/or medical illness that should be evaluated. Worsening of insomnia or the emergence of new thinking or behavior abnormalities may be the consequence of an unrecognized psychiatric or physical disorder. Such findings have emerged during the course of treatment with sedative/hypnotic drugs, including zolpidem.

5.4 Severe Anaphylactic and Anaphylactoid Reactions

Cases of angioedema involving the tongue, glottis or larynx have been reported in patients after taking the first or subsequent doses of sedative-hypnotics, including zolpidem. Some patients have had additional symptoms such as dyspnea, throat closing or nausea and vomiting that suggest anaphylaxis. Some patients have required medical therapy in the emergency department. If angioedema involves the throat, glottis or larynx, airway obstruction may occur and be fatal. Patients who develop angioedema after treatment with zolpidem should not be rechallenged with the drug.

5.5 Abnormal Thinking and Behavioral Changes

Abnormal thinking and behavior changes have been reported in patients treated with sedative/hypnotics, including AMBIEN. Some of these changes included decreased inhibition (e.g., aggressiveness and extroversion that seemed out of character), bizarre behavior, agitation and depersonalization. Visual and auditory hallucinations have been reported.

In controlled trials of AMBIEN 10 mg taken at bedtime <1% of adults with insomnia reported hallucinations. In a clinical trial, 7% of pediatric patients treated with AMBIEN 0.25 mg/kg taken at bedtime reported hallucinations versus 0% treated with placebo [see Use in Specific Populations (8.4)]. There have been postmarketing reports of delirium with zolpidem use [see Adverse Reactions (6.2)].

It can rarely be determined with certainty whether a particular instance of the abnormal behaviors listed above is drug induced, spontaneous in origin, or a result of an underlying psychiatric or physical disorder. Nonetheless, the emergence of any new behavioral sign or symptom of concern requires careful and immediate evaluation.

5.6 Use in Patients with Depression

In primarily depressed patients treated with sedative-hypnotics, worsening of depression, and suicidal thoughts and actions (including completed suicides), have been reported. Suicidal tendencies may be present in such patients and protective measures may be required. Intentional overdosage is more common in this group of patients; therefore, the lowest number of tablets that is feasible should be prescribed for the patient at any one time.

5.7 Respiratory Depression

Although studies with 10 mg zolpidem tartrate did not reveal respiratory depressant effects at hypnotic doses in healthy subjects or in patients with mild to moderate chronic obstructive pulmonary disease (COPD), a reduction in the Total Arousal Index, together with a reduction in lowest oxygen saturation and increase in the times of oxygen desaturation below 80% and 90%, was observed in patients with mild to moderate sleep apnea when treated with zolpidem compared to placebo. Since sedative-hypnotics have the capacity to depress respiratory drive, precautions should be taken if AMBIEN is prescribed to patients with compromised respiratory function or concomitant use with opioids or other CNS depressants. Postmarketing reports of respiratory insufficiency in patients receiving 10 mg of zolpidem tartrate, most of whom had pre-existing respiratory impairment, have been reported. The risk of respiratory depression should be considered prior to prescribing AMBIEN in patients with respiratory impairment including sleep apnea and myasthenia gravis or with concomitant opioid use [see Dosage and Administration (2.3), Drug Interactions (7.1)].

5.8 Precipitation of Hepatic Encephalopathy

Drugs affecting GABA receptors, such as zolpidem tartrate, have been associated with precipitation of hepatic encephalopathy in patients with hepatic insufficiency. In addition, patients with hepatic insufficiency do not clear zolpidem tartrate as rapidly as patients with normal hepatic function. Avoid AMBIEN use in patients with severe hepatic impairment as it may contribute to encephalopathy [see Dosage and Administration (2.2), Use in Specific Populations (8.7), Clinical Pharmacology (12.3)].

5.9 Withdrawal Effects

There have been reports of withdrawal signs and symptoms following the rapid dose decrease or abrupt discontinuation of zolpidem. Monitor patients for tolerance, abuse, and dependence [see Drug Abuse and Dependence (9.2, 9.3)].

6 ADVERSE REACTIONS

The following serious adverse reactions are discussed in greater detail in other sections of the labeling:

- Complex Sleep Behaviors [see Warnings and Precautions (5.1)]
- CNS-Depressant Effects and Next-Day Impairment [see Warnings and Precautions (5.2)]
- Severe Anaphylactic and Anaphylactoid Reactions [see Warnings and Precautions (5.4)]
- Abnormal Thinking and Behavior Changes [see Warnings and Precautions (5.5)]
- Withdrawal Effects [see Warnings and Precautions (5.9)]

6.1 Clinical Trials Experience

Associated with Discontinuation of Treatment

Approximately 4% of 1,701 patients who received zolpidem at all doses (1.25 to 90 mg) in U.S. premarketing clinical trials discontinued treatment because of an adverse reaction. Reactions most commonly associated with discontinuation from U.S. trials were daytime drowsiness (0.5%), dizziness (0.4%), headache (0.5%), nausea (0.6%), and vomiting (0.5%).

Approximately 4% of 1,959 patients who received zolpidem at all doses (1 to 50 mg) in similar foreign trials discontinued treatment because of an adverse reaction. Reactions most commonly associated with discontinuation from these trials were daytime drowsiness (1.1%), dizziness/vertigo (0.8%), amnesia (0.5%), nausea (0.5%), headache (0.4%), and falls (0.4%).

Data from a clinical study in which selective serotonin reuptake inhibitor (SSRI)-treated patients were given zolpidem revealed that four of the seven discontinuations during double-blind treatment with zolpidem (n=95) were associated with impaired concentration, continuing or aggravated depression, and manic reaction; one patient treated with placebo (n=97) was discontinued after an attempted suicide.

Most Commonly Observed Adverse Reactions in Controlled Trials

During short-term treatment (up to 10 nights) with AMBIEN at doses up to 10 mg, the most commonly observed adverse reactions associated with the use of zolpidem and seen at statistically significant differences from placebo-treated patients were drowsiness (reported by 2% of zolpidem patients), dizziness (1%), and diarrhea (1%). During longer-term treatment (28 to 35 nights) with zolpidem at doses up to 10 mg, the most commonly observed adverse reactions associated with the use of zolpidem and seen at statistically significant differences from placebo-treated patients were dizziness (5%) and drugged feelings (3%).

Adverse Reactions Observed at an Incidence of ≥1% in Controlled Trials

The following tables enumerate treatment-emergent adverse reactions frequencies that were observed at an incidence equal to 1% or greater among patients with insomnia who received zolpidem tartrate and at a greater incidence than placebo in U.S. placebo-controlled trials. Events reported by investigators were classified utilizing a modified World Health Organization (WHO) dictionary of preferred terms for the purpose of establishing event frequencies. The prescriber should be aware that these figures cannot be used to predict the incidence of side effects in the course of usual medical practice, in which patient characteristics and other factors differ from those that prevailed in these clinical trials. Similarly, the cited frequencies cannot be compared with figures obtained from other clinical investigators involving related drug products and uses, since each group of drug trials is conducted under a different set of conditions. However, the cited figures provide the physician with a basis for estimating the relative contribution of drug and nondrug factors to the incidence of side effects in the population studied.

The following table was derived from results of 11 placebo-controlled short-term U.S. efficacy trials involving zolpidem in doses ranging from 1.25 to 20 mg. The table is limited to data from doses up to and including 10 mg, the highest dose recommended for use.

Table 1: Incidences of Treatment-Emergent Adverse Reactions in Placebo-Controlled Clinical Trials Lasting up to 10 Nights (percentage of patients reporting)
Body System Adverse Reaction [Reactions reported by at least 1% of patients treated with AMBIEN and at a greater frequency than placebo.] | Zolpidem (≤10 mg) (N=685) | Placebo (N=473)
Central and Peripheral Nervous System
Headache | 7 | 6
Drowsiness | 2 | -
Dizziness | 1 | -
Gastrointestinal System
Diarrhea | 1 | -

The following table was derived from results of three placebo-controlled long-term efficacy trials involving AMBIEN (zolpidem tartrate). These trials involved patients with chronic insomnia who were treated for 28 to 35 nights with zolpidem at doses of 5, 10, or 15 mg. The table is limited to data from doses up to and including 10 mg, the highest dose recommended for use. The table includes only adverse events occurring at an incidence of at least 1% for zolpidem patients.

Table 2: Incidences of Treatment-Emergent Adverse Experiences in Placebo-Controlled Clinical Trials Lasting up to 35 Nights (percentage of patients reporting)
Body System Adverse Event [Reactions reported by at least 1% of patients treated with AMBIEN and at a greater frequency than placebo.] | Zolpidem (≤10 mg) (N=152) | Placebo (N=161)
Autonomic Nervous System
Dry mouth | 3 | 1
Body as a Whole
Allergy | 4 | 1
Back Pain | 3 | 2
Influenza-like symptoms | 2 | -
Chest pain | 1 | -
Cardiovascular System
Palpitation | 2 | -
Central and Peripheral Nervous System
Drowsiness | 8 | 5
Dizziness | 5 | 1
Lethargy | 3 | 1
Drugged feeling | 3 | -
Lightheadedness | 2 | 1
Depression | 2 | 1
Abnormal dreams | 1 | -
Amnesia | 1 | -
Sleep disorder | 1 | -
Gastrointestinal System
Diarrhea | 3 | 2
Abdominal pain | 2 | 2
Constipation | 2 | 1
Respiratory System
Sinusitis | 4 | 2
Pharyngitis | 3 | 1
Skin and Appendages
Rash | 2 | 1

Dose Relationship for Adverse Reactions

There is evidence from dose comparison trials suggesting a dose relationship for many of the adverse reactions associated with zolpidem use, particularly for certain CNS and gastrointestinal adverse events.

Adverse Event Incidence Across the Entire Preapproval Database

AMBIEN was administered to 3,660 subjects in clinical trials throughout the U.S., Canada, and Europe. Treatment-emergent adverse events associated with clinical trial participation were recorded by clinical investigators using terminology of their own choosing. To provide a meaningful estimate of the proportion of individuals experiencing treatment-emergent adverse events, similar types of untoward events were grouped into a smaller number of standardized event categories and classified utilizing a modified World Health Organization (WHO) dictionary of preferred terms.

The frequencies presented, therefore, represent the proportions of the 3,660 individuals exposed to zolpidem, at all doses, who experienced an event of the type cited on at least one occasion while receiving zolpidem. All reported treatment-emergent adverse events are included, except those already listed in the table above of adverse events in placebo-controlled studies, those coding terms that are so general as to be uninformative, and those events where a drug cause was remote. It is important to emphasize that, although the events reported did occur during treatment with AMBIEN, they were not necessarily caused by it.

Adverse events are further classified within body system categories and enumerated in order of decreasing frequency using the following definitions: frequent adverse events are defined as those occurring in greater than 1/100 subjects; infrequent adverse events are those occurring in 1/100 to 1/1,000 patients; rare events are those occurring in less than 1/1,000 patients.

Autonomic nervous system: Infrequent: increased sweating, pallor, postural hypotension, syncope. Rare: abnormal accommodation, altered saliva, flushing, glaucoma, hypotension, impotence, increased saliva, tenesmus.

Body as a whole: Frequent: asthenia. Infrequent: edema, falling, fatigue, fever, malaise, trauma. Rare: allergic reaction, allergy aggravated, anaphylactic shock, face edema, hot flashes, increased ESR, pain, restless legs, rigors, tolerance increased, weight decrease.

Cardiovascular system: Infrequent: cerebrovascular disorder, hypertension, tachycardia. Rare: angina pectoris, arrhythmia, arteritis, circulatory failure, extrasystoles, hypertension aggravated, myocardial infarction, phlebitis, pulmonary embolism, pulmonary edema, varicose veins, ventricular tachycardia.

Central and peripheral nervous system: Frequent: ataxia, confusion, euphoria, headache, insomnia, vertigo. Infrequent: agitation, anxiety, decreased cognition, detached, difficulty concentrating, dysarthria, emotional lability, hallucination, hypoesthesia, illusion, leg cramps, migraine, nervousness, paresthesia, sleeping (after daytime dosing), speech disorder, stupor, tremor. Rare: abnormal gait, abnormal thinking, aggressive reaction, apathy, appetite increased, decreased libido, delusion, dementia, depersonalization, dysphasia, feeling strange, hypokinesia, hypotonia, hysteria, intoxicated feeling, manic reaction, neuralgia, neuritis, neuropathy, neurosis, panic attacks, paresis, personality disorder, somnambulism, suicide attempts, tetany, yawning.

Gastrointestinal system: Frequent: dyspepsia, hiccup, nausea. Infrequent: anorexia, constipation, dysphagia, flatulence, gastroenteritis, vomiting. Rare: enteritis, eructation, esophagospasm, gastritis, hemorrhoids, intestinal obstruction, rectal hemorrhage, tooth caries.

Hematologic and lymphatic system: Rare: anemia, hyperhemoglobinemia, leukopenia, lymphadenopathy, macrocytic anemia, purpura, thrombosis.

Immunologic system: Infrequent: infection. Rare: abscess herpes simplex herpes zoster, otitis externa, otitis media.

Liver and biliary system: Infrequent: abnormal hepatic function, increased SGPT. Rare: bilirubinemia, increased SGOT.

Metabolic and nutritional: Infrequent: hyperglycemia, thirst. Rare: gout, hypercholesteremia, hyperlipidemia, increased alkaline phosphatase, increased BUN, periorbital edema.

Musculoskeletal system: Frequent: arthralgia, myalgia. Infrequent: arthritis. Rare: arthrosis, muscle weakness, sciatica, tendinitis.

Reproductive system: Infrequent: menstrual disorder, vaginitis. Rare: breast fibroadenosis, breast neoplasm, breast pain.

Respiratory system: Frequent: upper respiratory infection, lower respiratory infection. Infrequent: bronchitis, coughing, dyspnea, rhinitis. Rare: bronchospasm, respiratory depression, epistaxis, hypoxia, laryngitis, pneumonia.

Skin and appendages: Infrequent: pruritus. Rare: acne, bullous eruption, dermatitis, furunculosis, injection-site inflammation, photosensitivity reaction, urticaria.

Special senses: Frequent: diplopia, vision abnormal. Infrequent: eye irritation, eye pain, scleritis, taste perversion, tinnitus. Rare: conjunctivitis, corneal ulceration, lacrimation abnormal, parosmia, photopsia.

Urogenital system: Frequent: urinary tract infection. Infrequent: cystitis, urinary incontinence. Rare: acute renal failure, dysuria, micturition frequency, nocturia, polyuria, pyelonephritis, renal pain, urinary retention.

6.2 Postmarketing Experience

The following adverse reactions have been identified during postapproval use of AMBIEN. Because these reactions are reported voluntarily from a population of uncertain size, it is not always possible to reliably estimate their frequency or establish a causal relationship to drug exposure.

Liver and biliary system: acute hepatocellular, cholestatic or mixed liver injury with or without jaundice (i.e., bilirubin >2 × ULN, alkaline phosphatase ≥2 × ULN, transaminase ≥5 × ULN).

Psychiatric disorders: delirium

7 DRUG INTERACTIONS

7.1 CNS-Active Drugs

CNS Depressants

Coadministration of zolpidem with other CNS depressants increases the risk of CNS depression. Concomitant use of zolpidem with these drugs may increase drowsiness and psychomotor impairment, including impaired driving ability [see Warnings and Precautions (5.1, 5.2)]. Zolpidem tartrate was evaluated in healthy volunteers in single-dose interaction studies for several CNS drugs.

Alcohol

An additive adverse effect on psychomotor performance between alcohol and oral zolpidem was demonstrated [see Warnings and Precautions (5.1, 5.2)].

Opioids

The concomitant use of AMBIEN with opioids may increase the risk of respiratory depression. Limit dosage and duration of concomitant use of AMBIEN and opioids [see Dosage and Administration (2.3), Warnings and Precautions (5.7)].

Imipramine, Chlorpromazine

Imipramine in combination with zolpidem produced no pharmacokinetic interaction other than a 20% decrease in peak levels of imipramine, but there was an additive effect of decreased alertness. Similarly, chlorpromazine in combination with zolpidem produced no pharmacokinetic interaction, but there was an additive effect of decreased alertness and psychomotor performance [see Clinical Pharmacology (12.3)].

Sertraline

Concomitant administration of zolpidem and sertraline increases exposure to zolpidem [see Clinical Pharmacology (12.3)].

Fluoxetine

After multiple doses of zolpidem tartrate and fluoxetine an increase in the zolpidem half-life (17%) was observed. There was no evidence of an additive effect in psychomotor performance [see Clinical Pharmacology (12.3)].

Haloperidol

A study involving haloperidol and zolpidem revealed no effect of haloperidol on the pharmacokinetics or pharmacodynamics of zolpidem. The lack of a drug interaction following single-dose administration does not predict the absence of an effect following chronic administration [see Clinical Pharmacology (12.3)].

7.2 Drugs that Affect Drug Metabolism via Cytochrome P450

Some compounds known to induce or inhibit CYP3A may affect exposure to zolpidem. The effect of drugs that induce or inhibit other P450 enzymes on the exposure to zolpidem is not known.

CYP3A4 Inducers

Rifampin

Rifampin, a CYP3A4 inducer, significantly reduced the exposure to and the pharmacodynamic effects of zolpidem. Use of Rifampin in combination with zolpidem may decrease the efficacy of zolpidem and is not recommended [see Clinical Pharmacology (12.3)].

St. John's wort

Use of St. John's wort, a CYP3A4 inducer, in combination with zolpidem may decrease blood levels of zolpidem and is not recommended.

CYP3A4 Inhibitors

Ketoconazole

Ketoconazole, a potent CYP3A4 inhibitor, increased the exposure to and pharmacodynamic effects of zolpidem. Consideration should be given to using a lower dose of zolpidem when a potent CYP3A4 inhibitor and zolpidem are given together [see Clinical Pharmacology (12.3)].

8 USE IN SPECIFIC POPULATIONS

8.1 Pregnancy

Risk Summary

Neonates born to mothers using zolpidem late in the third trimester of pregnancy have been reported to experience symptoms of respiratory depression and sedation [see Clinical Considerations and Data]. Published data on the use of zolpidem during pregnancy have not reported a clear association with zolpidem and major birth defects [see Data]. Oral administration of zolpidem to pregnant rats and rabbits did not indicate a risk for adverse effects on fetal development at clinically relevant doses [see Data].

The estimated background risk of major birth defects and miscarriage for the indicated populations are unknown. All pregnancies have a background risk of birth defect, loss, or other adverse outcomes. In the U.S. general population, the estimated background risk of major birth defects and miscarriage in clinically recognized pregnancies is 2%–4% and 15%–20%, respectively.

Clinical Considerations

Fetal/neonatal adverse reactions

Zolpidem crosses the placenta and may produce respiratory depression and sedation in neonates. Monitor neonates exposed to AMBIEN during pregnancy and labor for signs of excess sedation, hypotonia, and respiratory depression and manage accordingly.

Data

Human data

Published data from observational studies, birth registries, and case reports on the use of zolpidem during pregnancy do not report a clear association with zolpidem and major birth defects.

There are limited postmarketing reports of severe to moderate cases of respiratory depression that occurred after birth in neonates whose mothers had taken zolpidem during pregnancy. These cases required artificial ventilation or intratracheal intubation. The majority of neonates recovered within hours to a few weeks after birth once treated.

Zolpidem has been shown to cross the placenta.

Animal data

Oral administration of zolpidem to pregnant rats during the period of organogenesis at 4, 20, and 100 mg base/kg/day, which are approximately 5, 25, and 120 times the maximum recommended human dose (MRHD) of 10 mg/day (8 mg zolpidem base) based on mg/m^2 body surface area, caused delayed fetal development (incomplete fetal skeletal ossification) at maternally toxic (ataxia) doses 25 and 120 times the MRHD based on mg/m^2 body surface area.

Oral administration of zolpidem to pregnant rabbits during the period of organogenesis at 1, 4, and 16 mg base/kg/day, which are approximately 2.5, 10, and 40 times the MRHD of 10 mg/day (8 mg zolpidem base) based on mg/m^2 body surface area caused embryo-fetal death and delayed fetal development (incomplete fetal skeletal ossification) at a maternally toxic (decreased body weight gain) dose 40 times the MRHD based on mg/m^2 body surface area.

Oral administration of zolpidem to pregnant rats from day 15 of gestation through lactation at 4, 20, and 100 mg base/kg/day, which are approximately 5, 25, and 120 times the MRHD of 10 mg/day (8 mg zolpidem base) based on mg/m^2 body surface area, delayed offspring growth and decreased survival at doses 25 and 120 times, respectively, the MRHD based on mg/m^2 body surface area.

8.2 Lactation

Risk Summary

Limited data from published literature report the presence of zolpidem in human milk. There are reports of excess sedation in infants exposed to zolpidem through breastmilk [see Clinical Considerations]. There is no information on the effects of zolpidem on milk production. The developmental and health benefits of breastfeeding should be considered along with the mother's clinical need for AMBIEN and any potential adverse effects on the breastfed infant from AMBIEN or from the underlying maternal condition.

Clinical Considerations

Infants exposed to AMBIEN through breastmilk should be monitored for excess sedation, hypotonia, and respiratory depression. A lactating woman may consider interrupting breastfeeding and pumping and discarding breast milk during treatment and for 23 hours (approximately 5 elimination half-lives) after AMBIEN administration in order to minimize drug exposure to a breast fed infant.

8.4 Pediatric Use

AMBIEN is not recommended for use in children. Safety and effectiveness of zolpidem in pediatric patients below the age of 18 years have not been established.

In an 8-week study in pediatric patients (aged 6–17 years) with insomnia associated with attention-deficit/hyperactivity disorder (ADHD) an oral solution of zolpidem tartrate dosed at 0.25 mg/kg at bedtime did not decrease sleep latency compared to placebo. Psychiatric and nervous system disorders comprised the most frequent (>5%) treatment emergent adverse reactions observed with zolpidem versus placebo and included dizziness (23.5% vs 1.5%), headache (12.5% vs 9.2%), and hallucinations were reported in 7% of the pediatric patients who received zolpidem; none of the pediatric patients who received placebo reported hallucinations [see Warnings and Precautions (5.5)]. Ten patients on zolpidem (7.4%) discontinued treatment due to an adverse reaction.

8.5 Geriatric Use

A total of 154 patients in U.S. controlled clinical trials and 897 patients in non-U.S. clinical trials who received zolpidem were ≥60 years of age. For a pool of U.S. patients receiving zolpidem at doses of ≤10 mg or placebo, there were three adverse reactions occurring at an incidence of at least 3% for zolpidem and for which the zolpidem incidence was at least twice the placebo incidence (i.e., they could be considered drug related).

Adverse Event | Zolpidem | Placebo
Dizziness | 3% | 0%
Drowsiness | 5% | 2%
Diarrhea | 3% | 1%

A total of 30/1,959 (1.5%) non-U.S. patients receiving zolpidem reported falls, including 28/30 (93%) who were ≥70 years of age. Of these 28 patients, 23 (82%) were receiving zolpidem doses >10 mg. A total of 24/1,959 (1.2%) non-U.S. patients receiving zolpidem reported confusion, including 18/24 (75%) who were ≥70 years of age. Of these 18 patients, 14 (78%) were receiving zolpidem doses >10 mg.

The dose of AMBIEN in elderly patients is 5 mg to minimize adverse effects related to impaired motor and/or cognitive performance and unusual sensitivity to sedative/hypnotic drugs [see Warnings and Precautions (5.2)].

8.6 Gender Difference in Pharmacokinetics

Women clear zolpidem tartrate from the body at a lower rate than men. Cmax and AUC parameters of zolpidem were approximately 45% higher at the same dose in female subjects compared with male subjects. Given the higher blood levels of zolpidem tartrate in women compared to men at a given dose, the recommended initial dose of AMBIEN for adult women is 5 mg, and the recommended dose for adult men is 5 or 10 mg.

In geriatric patients, clearance of zolpidem is similar in men and women. The recommended dose of AMBIEN in geriatric patients is 5 mg regardless of gender.

8.7 Hepatic Impairment

The recommended dose of AMBIEN in patients with mild to moderate hepatic impairment is 5 mg once daily immediately before bedtime. Avoid AMBIEN use in patients with severe hepatic impairment as it may contribute to encephalopathy [see Dosage and Administration (2.2), Warnings and Precautions (5.8), Clinical Pharmacology (12.3)].

9 DRUG ABUSE AND DEPENDENCE

9.1 Controlled Substance

Zolpidem tartrate is classified as a Schedule IV controlled substance by federal regulation.

9.2 Abuse

Abuse and addiction are separate and distinct from physical dependence and tolerance. Abuse is characterized by misuse of the drug for non-medical purposes, often in combination with other psychoactive substances. Tolerance is a state of adaptation in which exposure to a drug induces changes that result in a diminution of one or more of the drug effects over time. Tolerance may occur to both desired and undesired effects of drugs and may develop at different rates for different effects.

Addiction is a primary, chronic, neurobiological disease with genetic, psychosocial, and environmental factors influencing its development and manifestations. It is characterized by behaviors that include one or more of the following: impaired control over drug use, compulsive use, continued use despite harm, and craving. Drug addiction is a treatable disease, using a multidisciplinary approach, but relapse is common.

Studies of abuse potential in former drug abusers found that the effects of single doses of zolpidem tartrate 40 mg were similar, but not identical, to diazepam 20 mg, while zolpidem tartrate 10 mg was difficult to distinguish from placebo.

Because persons with a history of addiction to, or abuse of, drugs or alcohol are at increased risk for misuse, abuse and addiction of zolpidem, they should be monitored carefully when receiving zolpidem or any other hypnotic.

9.3 Dependence

Use of AMBIEN may lead to the development of physical and/or psychological dependence. The risk of dependence increases with dose and duration of treatment. The risk of abuse and dependence is also greater in patients with a history of alcohol or drug abuse. AMBIEN should be used with extreme caution in patients with current or past alcohol or drug abuse.

Physical dependence is a state of adaptation that is manifested by a specific withdrawal syndrome that can be produced by abrupt cessation, rapid dose reduction, decreasing blood level of the drug, and/or administration of an antagonist.

Sedative/hypnotics have produced withdrawal signs and symptoms following abrupt discontinuation. These reported symptoms range from mild dysphoria and insomnia to a withdrawal syndrome that may include abdominal and muscle cramps, vomiting, sweating, tremors, convulsions, and delirium.

The following adverse events, which are considered to meet the DSM-III-R criteria for uncomplicated sedative/hypnotic withdrawal, were reported during clinical trials with AMBIEN following placebo substitution occurring within 48 hours following last zolpidem treatment: fatigue, nausea, flushing, lightheadedness, uncontrolled crying, emesis, stomach cramps, panic attack, nervousness, and abdominal discomfort. These reported adverse events occurred at an incidence of 1% or less. However, available data cannot provide a reliable estimate of the incidence, if any, of dependence during treatment at recommended doses. There have been postmarketing reports of abuse, dependence and withdrawal with zolpidem.

10 OVERDOSAGE

10.1 Signs and Symptoms

In postmarketing experience of overdose with zolpidem tartrate alone, or in combination with CNS-depressant agents, impairment of consciousness ranging from somnolence to coma, cardiovascular and/or respiratory compromise, and fatal outcomes have been reported.

10.2 Recommended Treatment

General symptomatic and supportive measures should be used along with immediate gastric lavage where appropriate. Intravenous fluids should be administered as needed. Zolpidem's sedative hypnotic effect was shown to be reduced by flumazenil and therefore may be useful; however, flumazenil administration may contribute to the appearance of neurological symptoms (convulsions). As in all cases of drug overdose, respiration, pulse, blood pressure, and other appropriate signs should be monitored and general supportive measures employed. Hypotension and CNS depression should be monitored and treated by appropriate medical intervention. Sedating drugs should be withheld following zolpidem overdosage, even if excitation occurs. The value of dialysis in the treatment of overdosage has not been determined, although hemodialysis studies in patients with renal failure receiving therapeutic doses have demonstrated that zolpidem is not dialyzable.

As with the management of all overdosage, the possibility of multiple drug ingestion should be considered. The physician may wish to consider contacting a poison control center for up-to-date information on the management of hypnotic drug product overdosage.

11 DESCRIPTION

AMBIEN contains zolpidem tartrate, a gamma-aminobutyric acid (GABA) A receptor positive modulator of the imidazopyridine class. AMBIEN is available in 5 mg and 10 mg strength tablets for oral administration.

Chemically, zolpidem is N,N,6-trimethyl-2-p-tolylimidazo[1,2-a] pyridine-3-acetamide L-(+)-tartrate (2:1). It has the following structure:

Zolpidem tartrate is a white to off-white crystalline powder that is sparingly soluble in water, alcohol, and propylene glycol. It has a molecular weight of 764.88.

Each AMBIEN tablet includes the following inactive ingredients: hydroxypropyl methylcellulose, lactose, magnesium stearate, microcrystalline cellulose, polyethylene glycol, sodium starch glycolate, and titanium dioxide. The 5 mg tablet also contains FD&C Red No. 40, iron oxide colorant, and polysorbate 80.

12 CLINICAL PHARMACOLOGY

12.1 Mechanism of Action

Zolpidem is a GABA A receptor positive modulator presumed to exert its therapeutic effects in the short-term treatment of insomnia through binding to the benzodiazepine site of α1 subunit containing GABA A receptors, increasing the frequency of chloride channel opening resulting in the inhibition of neuronal excitation.

12.2 Pharmacodynamics

Zolpidem binds to GABA A receptors with greater affinity for α1 subunit relative to α2 and α3 subunit containing receptors. Zolpidem has no appreciable binding affinity for α5 subunit containing GABA A receptors. This binding profile may explain the relative absence of myorelaxant effects in animal studies. Zolpidem has no appreciable binding affinity for dopaminergic D2, serotonergic 5HT2, adrenergic, histaminergic or muscarinic receptors.

12.3 Pharmacokinetics

The pharmacokinetic profile of AMBIEN is characterized by rapid absorption from the gastrointestinal tract and a short elimination half-life (T1/2) in healthy subjects.

In a single-dose crossover study in 45 healthy subjects administered 5 and 10 mg zolpidem tartrate tablets, the mean peak concentrations (Cmax) were 59 (range: 29 to 113) and 121 (range: 58 to 272) ng/mL, respectively, occurring at a mean time (Tmax) of 1.6 hours for both. The mean AMBIEN elimination half-life was 2.6 (range: 1.4 to 4.5) and 2.5 (range: 1.4 to 3.8) hours, for the 5 and 10 mg tablets, respectively. AMBIEN is converted to inactive metabolites that are eliminated primarily by renal excretion. AMBIEN demonstrated linear kinetics in the dose range of 5 to 20 mg. Total protein binding was found to be 92.5 ± 0.1% and remained constant, independent of concentration between 40 and 790 ng/mL. Zolpidem did not accumulate in young adults following nightly dosing with 20 mg zolpidem tartrate tablets for 2 weeks.

A food-effect study in 30 healthy male subjects compared the pharmacokinetics of AMBIEN 10 mg when administered while fasting or 20 minutes after a meal. Results demonstrated that with food, mean AUC and Cmax were decreased by 15% and 25%, respectively, while mean Tmax was prolonged by 60% (from 1.4 to 2.2 hr). The half-life remained unchanged. These results suggest that, for faster sleep onset, AMBIEN should not be administered with or immediately after a meal.

Special Populations

Elderly

In the elderly, the dose for AMBIEN should be 5 mg [see Warnings and Precautions (5), Dosage and Administration (2)]. This recommendation is based on several studies in which the mean Cmax, T1/2, and AUC were significantly increased when compared to results in young adults. In one study of eight elderly subjects (>70 years), the means for Cmax, T1/2, and AUC significantly increased by 50% (255 vs 384 ng/mL), 32% (2.2 vs 2.9 hr), and 64% (955 vs 1,562 ng∙hr/mL), respectively, as compared to younger adults (20 to 40 years) following a single 20 mg oral dose. AMBIEN did not accumulate in elderly subjects following nightly oral dosing of 10 mg for 1 week.

Hepatic impairment

The pharmacokinetics of AMBIEN in eight patients with chronic hepatic insufficiency was compared to results in healthy subjects. Following a single 20 mg oral zolpidem tartrate dose, mean Cmax and AUC were found to be two times (250 vs 499 ng/mL) and five times (788 vs 4,203 ng∙hr/mL) higher, respectively, in hepatically compromised patients. Tmax did not change. The mean half-life in cirrhotic patients of 9.9 hr (range: 4.1 to 25.8 hr) was greater than that observed in normal subjects of 2.2 hr (range: 1.6 to 2.4 hr) [see Dosage and Administration (2.2), Warnings and Precautions (5.8), Use in Specific Populations (8.7)].

Renal impairment

The pharmacokinetics of zolpidem tartrate was studied in 11 patients with end-stage renal failure (mean ClCr = 6.5 ± 1.5 mL/min) undergoing hemodialysis three times a week, who were dosed with zolpidem tartrate 10 mg orally each day for 14 or 21 days. No statistically significant differences were observed for Cmax, Tmax, half-life, and AUC between the first and last day of drug administration when baseline concentration adjustments were made. Zolpidem was not hemodialyzable. No accumulation of unchanged drug appeared after 14 or 21 days. Zolpidem pharmacokinetics was not significantly different in renally impaired patients. No dosage adjustment is necessary in patients with compromised renal function.

Drug Interactions

CNS depressants

Coadministration of zolpidem with other CNS depressants increases the risk of CNS depression [see Warnings and Precautions (5.2)]. Zolpidem tartrate was evaluated in healthy volunteers in single-dose interaction studies for several CNS drugs. Imipramine in combination with zolpidem produced no pharmacokinetic interaction other than a 20% decrease in peak levels of imipramine, but there was an additive effect of decreased alertness. Similarly, chlorpromazine in combination with zolpidem produced no pharmacokinetic interaction, but there was an additive effect of decreased alertness and psychomotor performance.

A study involving haloperidol and zolpidem revealed no effect of haloperidol on the pharmacokinetics or pharmacodynamics of zolpidem. The lack of a drug interaction following single-dose administration does not predict the absence of an effect following chronic administration.

An additive adverse effect on psychomotor performance between alcohol and oral zolpidem was demonstrated [see Warnings and Precautions (5.2)].

Following five consecutive nightly doses at bedtime of oral zolpidem tartrate 10 mg in the presence of sertraline 50 mg (17 consecutive daily doses, at 7:00 am, in healthy female volunteers), zolpidem Cmax was significantly higher (43%) and Tmax was significantly decreased (-53%). Pharmacokinetics of sertraline and N-desmethylsertraline were unaffected by zolpidem.

A single-dose interaction study with zolpidem tartrate 10 mg and fluoxetine 20 mg at steady-state levels in male volunteers did not demonstrate any clinically significant pharmacokinetic or pharmacodynamic interactions. When multiple doses of zolpidem and fluoxetine were given at steady state and the concentrations evaluated in healthy females, an increase in the zolpidem half-life (17%) was observed. There was no evidence of an additive effect in psychomotor performance.

Drugs that affect drug metabolism via cytochrome P450

Some compounds known to inhibit CYP3A may increase exposure to zolpidem. The effect of inhibitors of other P450 enzymes on the pharmacokinetics of zolpidem is unknown.

A single-dose interaction study with zolpidem tartrate 10 mg and itraconazole 200 mg at steady-state levels in male volunteers resulted in a 34% increase in AUC0–∞ of zolpidem tartrate. There were no pharmacodynamic effects of zolpidem detected on subjective drowsiness, postural sway, or psychomotor performance.

A single-dose interaction study with zolpidem tartrate 10 mg and rifampin 600 mg at steady-state levels in female subjects showed significant reductions of the AUC (-73%), Cmax (-58%), and T1/2 (-36%) of zolpidem together with significant reductions in the pharmacodynamic effects of zolpidem tartrate. Rifampin, a CYP3A4 inducer, significantly reduced the exposure to and the pharmacodynamic effects of zolpidem [see Drug Interactions (7.2)].

Similarly, St. John's wort, a CYP3A4 inducer, may also decrease the blood levels of zolpidem.

A single-dose interaction study with zolpidem tartrate 5 mg and ketoconazole, a potent CYP3A4 inhibitor, given as 200 mg twice daily for 2 days increased Cmax of zolpidem (30%) and the total AUC of zolpidem (70%) compared to zolpidem alone and prolonged the elimination half-life (30%) along with an increase in the pharmacodynamic effects of zolpidem [see Drug Interactions (7.2)].

Additionally, fluvoxamine (a strong inhibitor of CYP1A2 and a weak inhibitor of CYP3A4 and CYP2C9) and ciprofloxacin (a strong inhibitor of CYP1A2 and a moderate inhibitor of CYP3A4) are also likely to inhibit zolpidem's metabolic pathways, potentially leading to an increase in zolpidem exposure.

Other drugs with no interactions with zolpidem

A study involving cimetidine/zolpidem tartrate and ranitidine/zolpidem tartrate combinations revealed no effect of either drug on the pharmacokinetics or pharmacodynamics of zolpidem.

Zolpidem tartrate had no effect on digoxin pharmacokinetics and did not affect prothrombin time when given with warfarin in healthy subjects.

13 NONCLINICAL TOXICOLOGY

13.1 Carcinogenesis, Mutagenesis, Impairment of Fertility

Carcinogenesis

Zolpidem was administered to mice and rats for 2 years at oral doses of 4, 18, and 80 mg base/kg/day. In mice, these doses are approximately 2.5, 10, and 50 times the MRHD of 10 mg/day (8 mg zolpidem base) based on mg/m^2 body surface area and in rats, these doses are approximately 5, 20, and 100 times the MRHD based on mg/m^2 body surface area. No evidence of carcinogenic potential was observed in mice. In rats, renal tumors (lipoma, liposarcoma) were seen at the mid and high doses.

Mutagenesis

Zolpidem was negative in in vitro (bacterial reverse mutation, mouse lymphoma, and chromosomal aberration) and in vivo (mouse micronucleus) genetic toxicology assays.

Impairment of Fertility

Zolpidem was administered to rats at 4, 20, and 100 mg base/kg/day, which are approximately 5, 25, and 120 times the MRHD of 10 mg/day (8 mg zolpidem base) based on mg/m^2 body surface area, prior to and during mating, and continuing in females through postpartum day 25. Zolpidem caused irregular estrus cycles and prolonged precoital intervals at the highest dose tested, which is approximately 120 times the MRHD based on mg/m^2 body surface area. The NOAEL for these effects is 25 times the MRHD based on a mg/m^2 body surface area. There was no impairment of fertility at any dose tested.

14 CLINICAL STUDIES

14.1 Transient Insomnia

Normal adults experiencing transient insomnia (n=462) during the first night in a sleep laboratory were evaluated in a double-blind, parallel group, single-night trial comparing two doses of zolpidem (7.5 and 10 mg) and placebo. Both zolpidem doses were superior to placebo on objective (polysomnographic) measures of sleep latency, sleep duration, and number of awakenings.

Normal elderly adults (mean age 68) experiencing transient insomnia (n=35) during the first two nights in a sleep laboratory were evaluated in a double-blind, crossover, 2-night trial comparing four doses of zolpidem (5, 10, 15 and 20 mg) and placebo. All zolpidem doses were superior to placebo on the two primary PSG parameters (sleep latency and efficiency) and all four subjective outcome measures (sleep duration, sleep latency, number of awakenings, and sleep quality).

14.2 Chronic Insomnia

Zolpidem was evaluated in two controlled studies for the treatment of patients with chronic insomnia (most closely resembling primary insomnia, as defined in the APA Diagnostic and Statistical Manual of Mental Disorders, DSM-IV™). Adult outpatients with chronic insomnia (n=75) were evaluated in a double-blind, parallel group, 5-week trial comparing two doses of zolpidem tartrate and placebo. On objective (polysomnographic) measures of sleep latency and sleep efficiency, zolpidem 10 mg was superior to placebo on sleep latency for the first 4 weeks and on sleep efficiency for weeks 2 and 4. Zolpidem was comparable to placebo on number of awakenings at both doses studied.

Adult outpatients (n=141) with chronic insomnia were also evaluated, in a double-blind, parallel group, 4-week trial comparing two doses of zolpidem and placebo. Zolpidem 10 mg was superior to placebo on a subjective measure of sleep latency for all 4 weeks, and on subjective measures of total sleep time, number of awakenings, and sleep quality for the first treatment week.

Increased wakefulness during the last third of the night as measured by polysomnography has not been observed in clinical trials with AMBIEN.

14.3 Studies Pertinent to Safety Concerns for Sedative/Hypnotic Drugs

Next-Day Residual Effects

Next-day residual effects of AMBIEN were evaluated in seven studies involving normal subjects. In three studies in adults (including one study in a phase advance model of transient insomnia) and in one study in elderly subjects, a small but statistically significant decrease in performance was observed in the Digit Symbol Substitution Test (DSST) when compared to placebo. Studies of AMBIEN in non-elderly patients with insomnia did not detect evidence of next-day residual effects using the DSST, the Multiple Sleep Latency Test (MSLT), and patient ratings of alertness.

Rebound Effects

There was no objective (polysomnographic) evidence of rebound insomnia at recommended doses seen in studies evaluating sleep on the nights following discontinuation of AMBIEN (zolpidem tartrate). There was subjective evidence of impaired sleep in the elderly on the first post-treatment night at doses above the recommended elderly dose of 5 mg.

Memory Impairment

Controlled studies in adults utilizing objective measures of memory yielded no consistent evidence of next-day memory impairment following the administration of AMBIEN. However, in one study involving zolpidem doses of 10 and 20 mg, there was a significant decrease in next-morning recall of information presented to subjects during peak drug effect (90 minutes post dose), i.e., these subjects experienced anterograde amnesia. There was also subjective evidence from adverse event data for anterograde amnesia occurring in association with the administration of AMBIEN, predominantly at doses above 10 mg.

Effects on Sleep Stages

In studies that measured the percentage of sleep time spent in each sleep stage, AMBIEN has generally been shown to preserve sleep stages. Sleep time spent in stages 3 and 4 (deep sleep) was found comparable to placebo with only inconsistent, minor changes in REM (paradoxical) sleep at the recommended dose.

16 HOW SUPPLIED/STORAGE AND HANDLING

AMBIEN 5 mg tablets are capsule-shaped, pink, film coated, with AMB 5 debossed on one side and 5401 on the other and supplied as:

NDC Number | Size
0024-5401-31 | bottle of 100

AMBIEN 10 mg tablets are capsule-shaped, white, film coated, with AMB 10 debossed on one side and 5421 on the other and supplied as:

NDC Number | Size
0024-5421-31 | bottle of 100

STORAGE AND HANDLING

Store at controlled room temperature 20°C–25°C (68°F–77°F).

17 PATIENT COUNSELING INFORMATION

Advise the patient to read the FDA-approved patient labeling (Medication Guide).

Inform patients and their families about the benefits and risks of treatment with AMBIEN. Inform patients of the availability of a Medication Guide and instruct them to read the Medication Guide prior to initiating treatment with AMBIEN and with each prescription refill. Review the AMBIEN Medication Guide with every patient prior to initiation of treatment. Instruct patients or caregivers that AMBIEN should be taken only as prescribed.

Complex Sleep Behaviors

Instruct patients and their families that AMBIEN may cause complex sleep behaviors, including sleep-walking, sleep-driving, preparing and eating food, making phone calls, or having sex while not being fully awake. Serious injuries and death have occurred during complex sleep behavior episodes. Tell patients to discontinue AMBIEN and notify their healthcare provider immediately if they develop any of these symptoms [see Boxed Warning, Warnings and Precautions (5.1)].

CNS-Depressant Effects and Next-Day Impairment

Tell patients that AMBIEN has the potential to cause next-day impairment, and that this risk is increased if dosing instructions are not carefully followed. Tell patients to wait for at least 8 hours after dosing before driving or engaging in other activities requiring full mental alertness. Inform patients that impairment can be present despite feeling fully awake. Advise patients that increased drowsiness and decreased consciousness may increase the risk of falls in some patients [see Warnings and Precautions (5.2)].

Severe Anaphylactic and Anaphylactoid Reactions

Inform patients that severe anaphylactic and anaphylactoid reactions have occurred with zolpidem. Describe the signs/symptoms of these reactions and advise patients to seek medical attention immediately if any of them occur [see Warnings and Precautions (5.4)].

Suicide

Tell patients to immediately report any suicidal thoughts.

Alcohol and other Drugs

Ask patients about alcohol consumption, medicines they are taking, and drugs they may be taking without a prescription. Advise patients not to use AMBIEN if they drank alcohol that evening or before bed.

Concomitant Use with Opioids

Inform patients and caregivers that potentially serious additive effects may occur if AMBIEN is used with opioids and not to use such drugs concomitantly unless supervised by a healthcare provider [see Warnings and Precautions (5.2, 5.7), Drug Interactions (7.1)].

Tolerance, Abuse, and Dependence

Tell patients not to increase the dose of AMBIEN on their own, and to inform you if they believe the drug "does not work."

Administration Instructions

Patients should be counseled to take AMBIEN right before they get into bed and only when they are able to stay in bed a full night (7–8 hours) before being active again. AMBIEN tablets should not be taken with or immediately after a meal. Advise patients NOT to take AMBIEN if they drank alcohol that evening.

Pregnancy

Advise patients to notify their healthcare provider if they become pregnant or intend to become pregnant during treatment with AMBIEN. Advise patients that use of AMBIEN late in the third trimester may cause respiratory depression and sedation in neonates. Advise mothers who used AMBIEN during the late third trimester of pregnancy to monitor neonates for signs of sleepiness (more than usual), breathing difficulties, or limpness [see Use in Specific Populations (8.1)].

Lactation

Advise breastfeeding mothers using AMBIEN to monitor infants for increased sleepiness, breathing difficulties, or limpness. Instruct breastfeeding mothers to seek immediate medical care if they notice these signs. A lactating woman may consider pumping and discarding breastmilk during treatment and for 23 hours after AMBIEN administration to minimize drug exposure to a breastfed infant [see Use in Specific Populations (8.2)].

Manufactured by:
sanofi-aventis U.S. LLC
Bridgewater, NJ 08807
A SANOFI COMPANY

MEDICATION GUIDE
AMBIEN (ām'bē-ən)
(zolpidem tartrate)
tablets, for oral use, C-IV

What is the most important information I should know about AMBIEN?
AMBIEN may cause serious side effects, including:

- Complex sleep behaviors. After taking AMBIEN, you may get up out of bed while not being fully awake and do an activity that you do not know you are doing. The next morning, you may not remember that you did anything during the night. These activities may happen with AMBIEN whether or not you drink alcohol or take other medicines that make you sleepy. Some of these complex sleep behaviors have caused serious injury and death. People taking AMBIEN have reported:
  - sleep-walking
  - sleep-driving
  - making and eating food
  - talking on the phone
  - having sex
  Stop taking ABMIEN and tell your healthcare provider right away if you find out that you have done any of the above activities after taking AMBIEN.

What is AMBIEN?
AMBIEN is a prescription sleep medicine used for the short-term treatment of adults who have trouble falling asleep (insomnia).

- It is not known if AMBIEN is safe and effective in children under the age of 18 years. AMBIEN is not recommended for use in children under the age of 18 years.
- AMBIEN is a federally controlled substance (C-IV) because it can be abused or lead to dependence. Keep AMBIEN in a safe place to protect it from theft. Never give your AMBIEN to anyone else because it may cause death or harm them. Selling or giving away this medicine is against the law.

Do not take AMBIEN if you:

- have had complex sleep behaviors that happened after taking AMBIEN in the past. See "What is the most important information I should know about AMBIEN?"
- are allergic to zolpidem or any of the ingredients in AMBIEN. See the end of this Medication Guide for a complete list of ingredients in AMBIEN.

Before taking AMBIEN, tell your healthcare provider about all of your medical conditions, including if you:

- have a history of depression, mental illness, or suicidal thoughts or actions
- have a history of drug or alcohol abuse or addiction
- have kidney or liver disease
- have a lung disease or breathing problems
- have sleep apnea
- have myasthenia gravis
- are pregnant or plan to become pregnant. Taking AMBIEN in the third trimester of pregnancy may harm your unborn baby.
  - Tell your healthcare provider if you become pregnant or plan to become pregnant during treatment with AMBIEN.
  - Babies born to mothers who take AMBIEN during the third trimester of pregnancy may have symptoms of breathing problems and sedation (such as sleepiness or low muscle tone).
- are breastfeeding or plan to breastfeed. AMBIEN passes into your breast milk and may harm your baby. Talk to your healthcare provider about the best way to feed your baby during treatment with AMBIEN.

Tell your healthcare provider about all of the medicines you take, including prescription and over-the-counter medicines, vitamins, and herbal supplements. AMBIEN and other medicines can interact with each other causing serious side effects. AMBIEN may affect the way other medicines work, and other medicines may affect how AMBIEN works.
Especially tell your healthcare provider if you:

- take benzodiazepines
- take opioids as it may increase the risk of breathing problems (respiratory depression)
- take tricyclic antidepressants
- take other medicines that can make you sleepy or affect your breathing (including other zolpidem medicines)
- drink alcohol

You can ask your pharmacist for a list of medicines that interact with AMBIEN.
Know the medicines you take. Keep a list of them to show your healthcare provider and pharmacist when you get a new medicine.

How should I take AMBIEN?

- Take AMBIEN exactly as prescribed. Do not change your dose on your own. Tell your healthcare provider if you think AMBIEN is not working for you.
- AMBIEN is for short-term use only. Treatment with AMBIEN should be as short as possible because the risk of dependence increases the longer you are being treated.
- Take 1 AMBIEN tablet at night right before bedtime.
- Do not take AMBIEN if you are not able to stay in bed a full night (7 to 8 hours) before you must be active again.
- You should not take AMBIEN with or right after a meal. AMBIEN may help you fall asleep faster if you take it on an empty stomach.
- Do not take AMBIEN if you drank alcohol that evening or before bed.
- Call your healthcare provider if your sleep problems get worse or do not get better within 7 to 10 days. This may mean that there is another condition causing your sleep problems.
- If you take too much AMBIEN, call your healthcare provider or go to the nearest hospital emergency room right away.

What are the possible side effects of AMBIEN?
AMBIEN may cause serious side effects, including:

- See "What is the most important information I should know about AMBIEN?"
- AMBIEN can make you sleepy or dizzy and can slow your thinking and motor skills. Because AMBIEN can make you sleepy or dizzy you are at a higher risk for falls.
  - Do not drive, operate heavy machinery, or do other dangerous activities until you know how AMBIEN affects you.
  - Do not drink alcohol or take opioids or other medicines that may make you sleepy or dizzy while taking AMBIEN without first talking to your healthcare provider. When taken with alcohol or other medicines that cause sleepiness or dizziness, AMBIEN may make your sleepiness or dizziness much worse.
- Severe allergic reactions. Symptoms include swelling of the tongue or throat, trouble breathing, and nausea and vomiting. Get emergency medical help right away if you develop any of these symptoms during treatment with AMBIEN.
- Abnormal thoughts and behavior. Symptoms include more outgoing or aggressive behavior than normal, confusion (delirium), acting strangely, agitation, hallucinations, worsening of depression, and suicidal thoughts or actions.
- Risk of suicide and worsening of depression. Worsening of depression, including suicidal thoughts and actions can happen during treatment with medicines like AMBIEN. Call your healthcare provider right away if you develop any thoughts of suicide, dying, or worsening depression during treatment with AMBIEN.
- Breathing problems. See "Before taking AMBIEN, tell your healthcare provider about all of your medical conditions, including if you:" Call your healthcare provider or get emergency medical help right away if you develop breathing problems during treatment with AMBIEN.
- Problems with your nervous system caused by severe liver disease (hepatic encephalopathy).
- Withdrawal symptoms. You may have withdrawal symptoms if you stop taking AMBIEN suddenly. Withdrawal symptoms can be serious and include stomach and muscle cramps, vomiting, sweating, shakiness, seizures, and confusion (delirium). Talk to your healthcare provider about slowly stopping AMBIEN to avoid withdrawal symptoms.

The most common side effects of AMBIEN include sleepiness, dizziness, diarrhea, and grogginess or feeling like you have been drugged.
These are not all the side effects of AMBIEN.
Call your doctor for medical advice about side effects. You may report side effects to FDA at 1-800-FDA-1088.

How should I store AMBIEN?

- Store AMBIEN at room temperature between 68°F to 77°F (20°C to 25°C).

Keep AMBIEN and all medicines out of reach of children.

General Information about the safe and effective use of AMBIEN.
Medicines are sometimes prescribed for purposes other than those listed in a Medication Guide. Do not use AMBIEN for a condition for which it was not prescribed. Do not give AMBIEN to other people, even if they have the same symptoms that you have. It may harm them. You can ask your healthcare provider or pharmacist for information about AMBIEN that is written for healthcare professionals.

What are the ingredients in AMBIEN?
Active Ingredient: zolpidem tartrate
Inactive Ingredients: hydroxypropyl methylcellulose, lactose, magnesium stearate, microcrystalline cellulose, polyethylene glycol, sodium starch glycolate, and titanium dioxide. In addition, the 5 mg tablet contains FD&C Red No. 40, iron oxide colorant, and polysorbate 80.
Manufactured by:
sanofi-aventis U.S. LLC
Bridgewater, NJ 08807
A SANOFI COMPANY
© 2022 sanofi-aventis U.S. LLC
For more information, go to WWW.AMBIEN.com or call 1-800-633-1610.

This Medication Guide has been approved by the U.S. Food and Drug Administration.

Revised: 2/2022

PRINCIPAL DISPLAY PANEL - 5 mg Tablet Bottle Label

A-031
NDC 0024-5401-31

AMBIEN® CIV
(ZOLPIDEM TARTRATE)

5 mg

Dispense with
Medication Guide

Rx only

100 Tablets

SANOFI

PRINCIPAL DISPLAY PANEL - 10 mg Tablet Bottle Label

A-231
NDC 0024-5421-31

AMBIEN® CIV
(ZOLPIDEM TARTRATE)

10 mg

Dispense with
Medication Guide

Rx only

100 Tablets

SANOFI